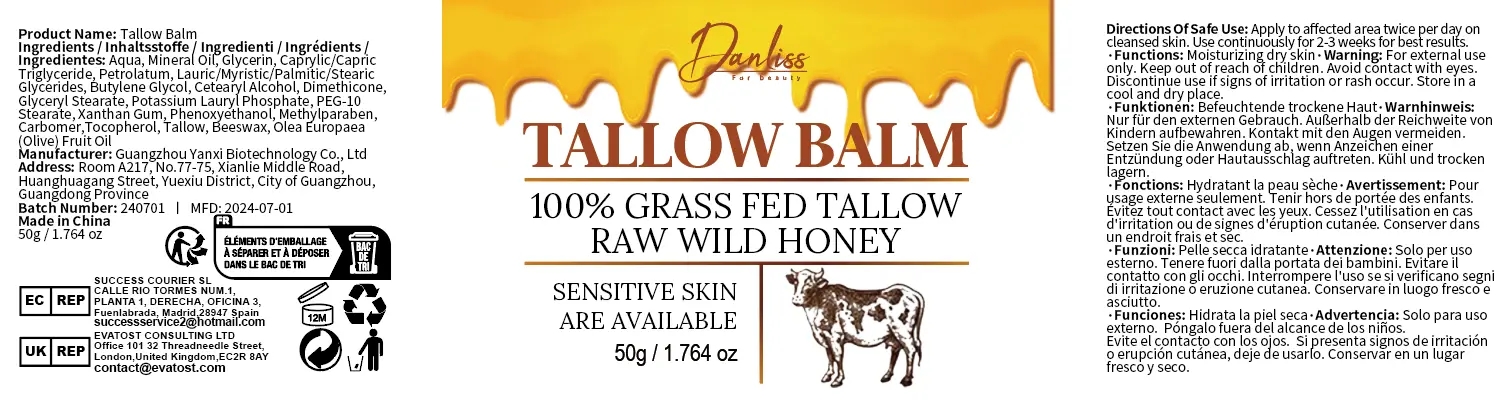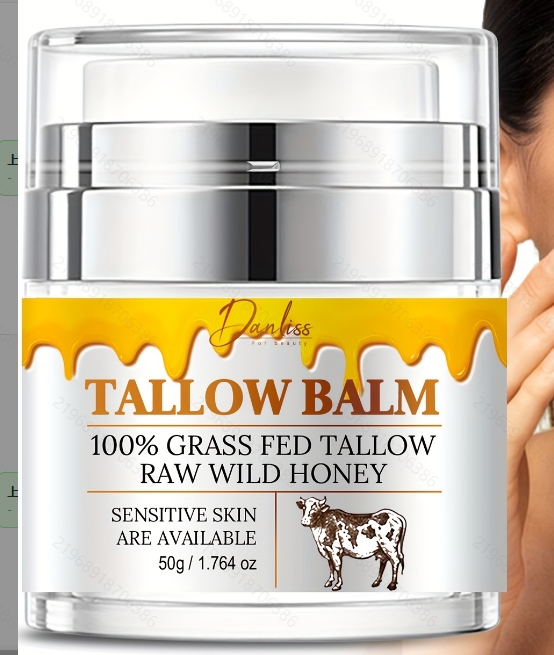 DRUG LABEL: Tallow Balm
NDC: 84025-202 | Form: CREAM
Manufacturer: Guangzhou Yanxi Biotechnology Co., Ltd
Category: otc | Type: HUMAN OTC DRUG LABEL
Date: 20241008

ACTIVE INGREDIENTS: GLYCERIN 3 mg/100 mL; MINERAL OIL 5 mg/100 mL
INACTIVE INGREDIENTS: WATER

DOSAGE AND ADMINISTRATION

use as a normal face care

WARNINGS

keep out of children

INACTIVE INGREDIENT

Aqua

INDICATIONS AND USAGE

for face care

keep out of children

PURPOSE

For moisturizing the face